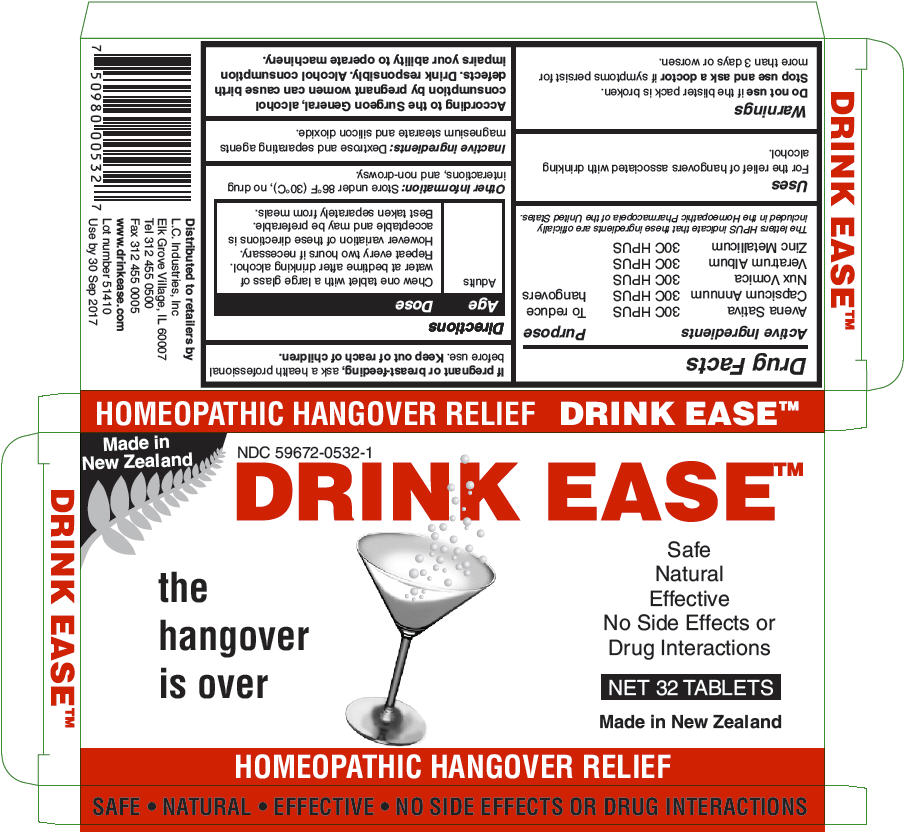 DRUG LABEL: Drink Ease
NDC: 59672-0532 | Form: TABLET
Manufacturer: LC Industries
Category: homeopathic | Type: HUMAN OTC DRUG LABEL
Date: 20140814

ACTIVE INGREDIENTS: Avena Sativa Flowering Top 30 [hp_C]/1 1; Capsicum 30 [hp_C]/1 1; Strychnos Nux-Vomica Seed 30 [hp_C]/1 1; Veratrum Album Root 30 [hp_C]/1 1; Zinc 30 [hp_C]/1 1
INACTIVE INGREDIENTS: Dextrose 242 mg/1 1; Silicon Dioxide; Magnesium stearate

DRINK EASE™

Drug Facts

ACTIVE INGREDIENT

Active Ingredients |  | Purpose
Avena Sativa | 30C HPUS | To reduce hangovers
Capsicum Annuum | 30C HPUS | To reduce hangovers
Nux Vomica | 30C HPUS | To reduce hangovers
Veratrum Album | 30C HPUS | To reduce hangovers
Zinc Metallicum | 30C HPUS
The letters HPUS indicate that these ingredients are officially included in the Homeopathic Pharmacopeia of the United States.

Uses

For the relief of hangovers associated with drinking alcohol.

Warnings

Do not use if the blister pack is broken.

Stop use and ask a doctor if symptoms persist for more than 3 days or worsen.

PREGNANCY OR BREAST FEEDING

If pregnant or breast-feeding, ask a health professional before use.

Keep out of reach of children.

Directions

Age | Dose
Adults | Chew one tablet with a large glass of water at bedtime after drinking alcohol. Repeat every two hours if necessary. However variation of these directions is acceptable and may be preferable. Best taken separately from meals.

Other Information

Store under 86°F (30°C), no drug interactions, and non-drowsy.

Inactive ingredients

Dextrose and separating agents magnesium stearate and silicon dioxide.

According to the Surgeon General, alcohol consumption by pregnant women can cause birth defects. Drink responsibly. Alcohol consumption impairs your ability to operate machinery.

Distributed to retailers by
L.C. Industries, Inc
Elk Grove Village, IL 60007

PRINCIPAL DISPLAY PANEL - 32 Tablet Blister Pack Carton

Made in
New Zealand

NDC 59672-0532-1
DRINK EASE™

the
hangover
is over

Safe
Natural
Effective
No Side Effects or
Drug Interactions

NET 32 TABLETS

Made in New Zealand

HOMEOPATHIC HANGOVER RELIEF